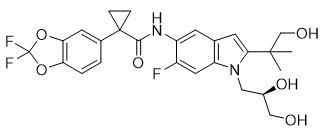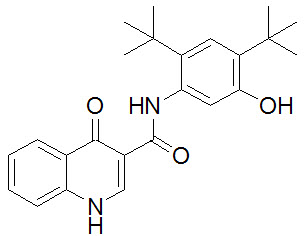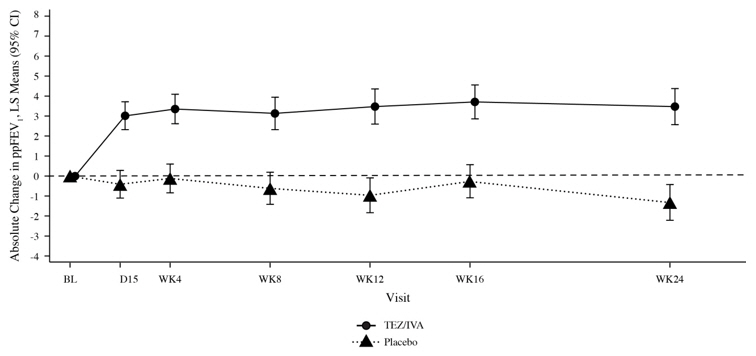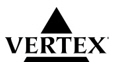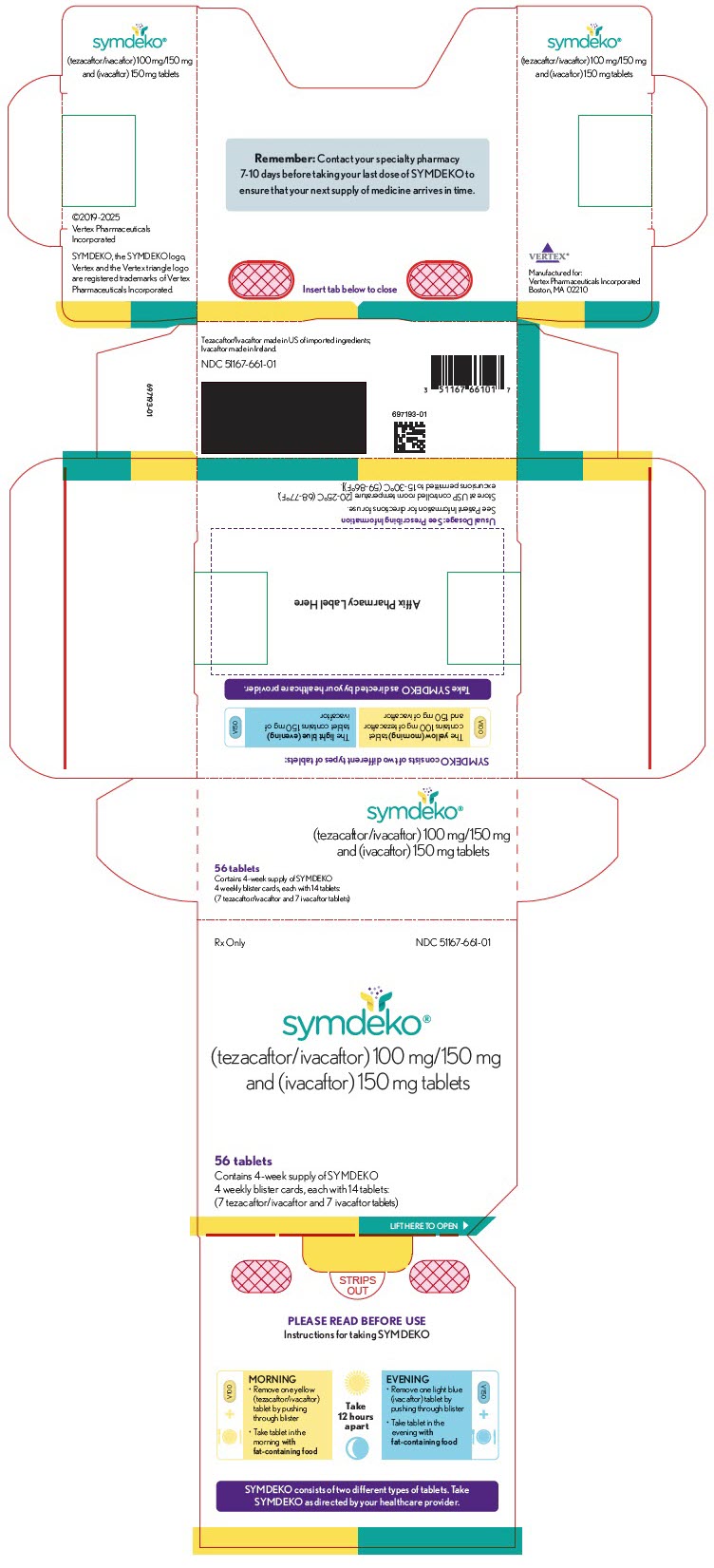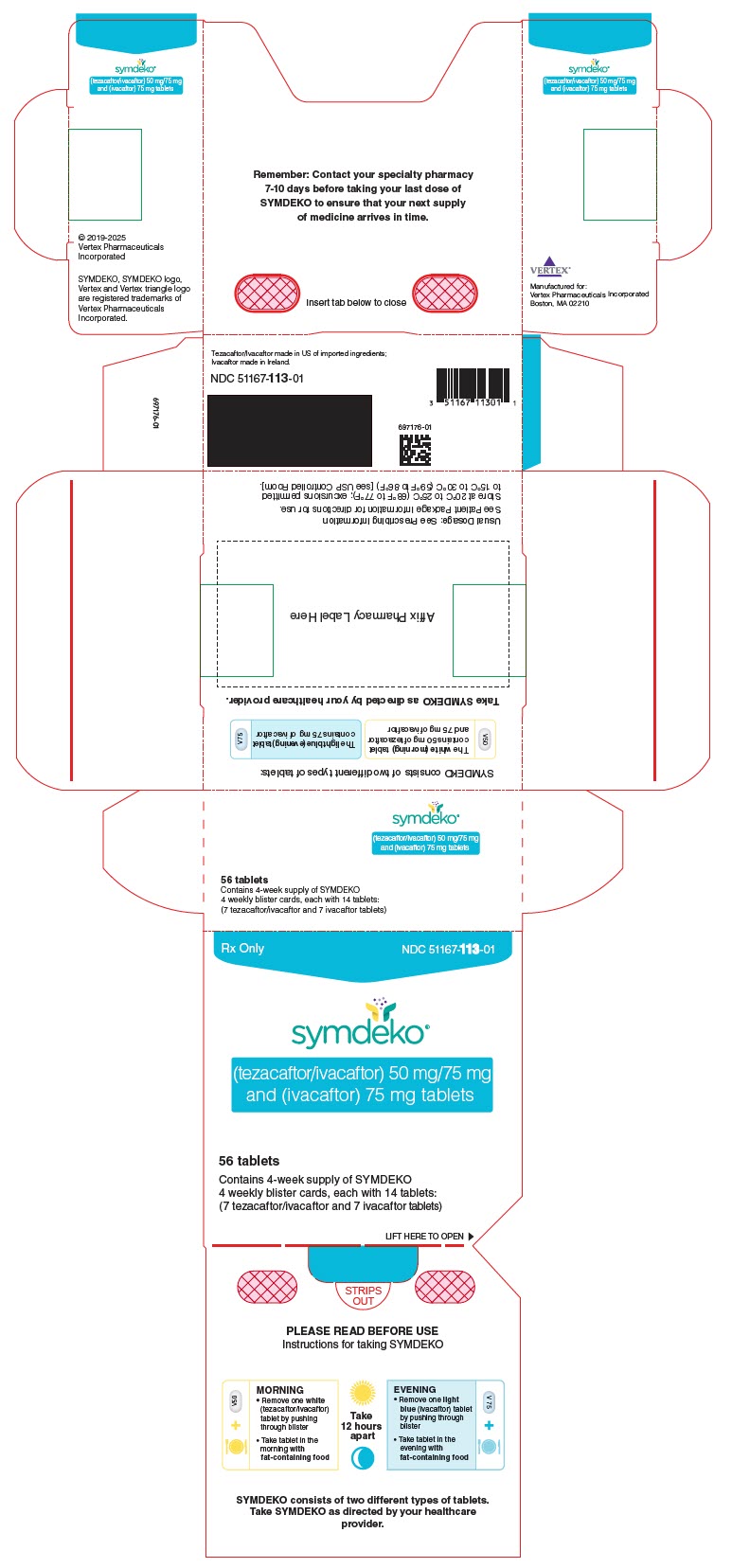 DRUG LABEL: SYMDEKO
NDC: 51167-661 | Form: KIT | Route: ORAL
Manufacturer: Vertex Pharmaceuticals Incorporated
Category: prescription | Type: HUMAN PRESCRIPTION DRUG LABEL
Date: 20250930

ACTIVE INGREDIENTS: Tezacaftor 100 mg/1 1; Ivacaftor 150 mg/1 1; Ivacaftor 150 mg/1 1
INACTIVE INGREDIENTS: HYPROMELLOSE ACETATE SUCCINATE 06081224 (3 MPA.S); Sodium lauryl sulfate; HYPROMELLOSE, UNSPECIFIED; MICROCRYSTALLINE CELLULOSE; Croscarmellose sodium; MAGNESIUM STEARATE; HYDROXYPROPYL CELLULOSE, UNSPECIFIED; Titanium dioxide; Talc; FERRIC OXIDE YELLOW; HYPROMELLOSE 2910 (6 MPA.S); SILICON DIOXIDE; CROSCARMELLOSE SODIUM; HYPROMELLOSE ACETATE SUCCINATE 06081224 (3 MPA.S); LACTOSE MONOHYDRATE; MAGNESIUM STEARATE; MICROCRYSTALLINE CELLULOSE; SODIUM LAURYL SULFATE; CARNAUBA WAX; FD&C Blue No. 2; POLYETHYLENE GLYCOL 3350; POLYVINYL ALCOHOL, UNSPECIFIED; TALC; TITANIUM DIOXIDE; AMMONIA; FERROSOFERRIC OXIDE; PROPYLENE GLYCOL; SHELLAC

HIGHLIGHTS OF PRESCRIBING INFORMATION

These highlights do not include all the information needed to use SYMDEKO safely and effectively. See full prescribing information for SYMDEKO.
SYMDEKO® (tezacaftor/ivacaftor) tablets; (ivacaftor) tablets, for oral use
Initial U.S. Approval: 2018

RECENT MAJOR CHANGES

Warnings and Precautions, Intracranial Hypertension (5.3) | 09/2025

1 INDICATIONS AND USAGE

SYMDEKO is a combination of tezacaftor and ivacaftor, indicated for the treatment of cystic fibrosis (CF) in patients aged 6 years and older who are homozygous for the F508del mutation or who have at least one mutation in the cystic fibrosis transmembrane conductance regulator (CFTR) gene that is responsive to tezacaftor/ivacaftor based on in vitro data and/or clinical evidence. (12.1, 14)

If the patient's genotype is unknown, an FDA-cleared CF mutation test should be used to detect the presence of a CFTR mutation followed by verification with bi-directional sequencing when recommended by the mutation test instructions for use. (1)

2 DOSAGE AND ADMINISTRATION

- Pediatric patients aged 6 to less than 12 years weighing less than 30 kg: one tablet (containing tezacaftor 50 mg/ivacaftor 75 mg) in the morning and one tablet (containing ivacaftor 75 mg) in the evening, approximately 12 hours apart. SYMDEKO should be taken with fat-containing food. (2.1, 2.2, 12.3)
- Adults and pediatric patients aged 12 years and older or pediatric patients aged 6 to less than 12 years weighing 30 kg or more: one tablet (containing tezacaftor 100 mg/ivacaftor 150 mg) in the morning and one tablet (containing ivacaftor 150 mg) in the evening, approximately 12 hours apart. SYMDEKO should be taken with fat-containing food. (2.1, 2.2, 12.3)
- Reduce dosage in patients with moderate and severe hepatic impairment. (2.3, 8.6, 12.3)
- See full prescribing information for dosage modifications due to drug interactions with SYMDEKO. (2.4, 7.2, 12.3)

3 DOSAGE FORMS AND STRENGTHS

- Tablets: tezacaftor 50 mg/ivacaftor 75 mg fixed-dose combination tablets co-packaged with ivacaftor 75 mg tablets. (3)
- Tablets: tezacaftor 100 mg/ivacaftor 150 mg fixed-dose combination tablets co-packaged with ivacaftor 150 mg tablets. (3)

4 CONTRAINDICATIONS

- None. (4)

5 WARNINGS AND PRECAUTIONS

- Elevated transaminases (ALT or AST): Transaminases (ALT and AST) should be assessed prior to initiating SYMDEKO, every 3 months during the first year of treatment, and annually thereafter. In patients with a history of transaminase elevations, more frequent monitoring should be considered. Dosing should be interrupted in patients with significant elevations of transaminases, e.g., patients with ALT or AST >5 × upper limit of normal (ULN), or ALT or AST >3 × ULN with bilirubin >2 × ULN. Following resolution of transaminase elevations, consider the benefits and risks of resuming treatment. (5.1, 6)
- Hypersensitivity reactions: Anaphylaxis has been reported with SYMDEKO in the postmarketing setting. Initiate appropriate therapy in the event of a hypersensitivity reaction. (5.2)
- Intracranial hypertension: Intracranial hypertension (IH) has been reported in the postmarketing setting with the use of drugs containing the same or similar active ingredients as SYMDEKO. If an unusual headache or visual disturbances occur during treatment, and IH is suspected, interrupt SYMDEKO and refer for prompt medical evaluation. (5.3)
- Use with CYP3A inducers: Concomitant use with strong CYP3A inducers (e.g., rifampin, St. John's wort) substantially decrease exposure of ivacaftor and may decrease the exposure of tezacaftor, which may reduce therapeutic effectiveness. Therefore, co-administration is not recommended. (5.4, 7.1, 12.3)
- Cataracts: Non-congenital lens opacities/cataracts have been reported in pediatric patients treated with SYMDEKO. Baseline and follow-up examinations are recommended in pediatric patients initiating SYMDEKO treatment. (5.5, 8.4)

6 ADVERSE REACTIONS

The most common adverse drug reactions to SYMDEKO (occurring in ≥3% of patients) were headache, nausea, sinus congestion, and dizziness. (6.1)

To report SUSPECTED ADVERSE REACTIONS, contact Vertex Pharmaceuticals Incorporated at 1-877-634-8789 or FDA at 1-800-FDA-1088 or www.fda.gov/medwatch.

7 DRUG INTERACTIONS

CYP3A inhibitors: Reduce SYMDEKO dosage when co-administered with strong (e.g., ketoconazole) or moderate (e.g., fluconazole) CYP3A inhibitors. Avoid food containing grapefruit. (2.4, 7.2, 12.3)

FULL PRESCRIBING INFORMATION

1 INDICATIONS AND USAGE

SYMDEKO is indicated for the treatment of cystic fibrosis (CF) in patients aged 6 years and older who are homozygous for the F508del mutation or who have at least one mutation in the cystic fibrosis transmembrane conductance regulator (CFTR) gene that is responsive to tezacaftor/ivacaftor based on in vitro data and/or clinical evidence [see Clinical Pharmacology (12.1) and Clinical Studies (14)].

If the patient's genotype is unknown, an FDA-cleared CF mutation test should be used to detect the presence of a CFTR mutation followed by verification with bi-directional sequencing when recommended by the mutation test instructions for use.

2 DOSAGE AND ADMINISTRATION

2.1 General Dosage Information

Swallow the tablets whole.

SYMDEKO should be taken with fat-containing food, such as food recommended in standard nutritional guidelines. Examples of meals or snacks that contain fat are those prepared with butter or oils or those containing eggs, cheeses, nuts, whole milk, or meats, etc. [see Clinical Pharmacology (12.3)].

2.2 Recommended Dosage in Adults, Adolescents, and Children Aged 6 Years and Older

Adults, adolescents, and children aged 6 years and older should be dosed according to Table 1. The morning and the evening doses should be taken approximately 12 hours apart.

Table 1: Recommended Dosage for Patients Aged 6 Years and Older
Age | Morning (one tablet) | Evening (one tablet)
6 to <12 years weighing <30 kg | tezacaftor 50 mg/ivacaftor 75 mg | ivacaftor 75 mg
6 to <12 years weighing ≥30 kg | tezacaftor 100 mg/ivacaftor 150 mg | ivacaftor 150 mg
≥12 years | tezacaftor 100 mg/ivacaftor 150 mg | ivacaftor 150 mg

Information for Missed Doses:

If 6 hours or less have passed since the missed morning or evening dose, the patient should take the missed dose as soon as possible and continue on the original schedule. If more than 6 hours have passed since the missed morning or evening dose, the patient should not take the missed dose. The next scheduled dose can be taken at the usual time. More than one dose should not be taken at the same time.

2.3 Recommended Dosage for Patients with Hepatic Impairment

For dosage adjustment for patients with hepatic impairment, refer to Table 2.

Studies have not been conducted in patients with severe hepatic impairment (Child-Pugh Class C), but exposure of tezacaftor and ivacaftor is expected to be higher than in patients with moderate hepatic impairment. Therefore, SYMDEKO should be used with caution at an adjusted dosage after weighing the risks and benefits of treatment in these patients [see Use in Specific Populations (8.6), Clinical Pharmacology (12.3), and Patient Counseling Information (17)].

Table 2: Recommended Dosage for Patients with Hepatic Impairment
Hepatic Impairment | Morning |  | Evening
Hepatic Impairment | Patients Aged 6 to <12 Years Weighing <30 kg | Patients Aged 6 to <12 Years Weighing ≥30 kg and Patients Age ≥12 Years | All Patients
Mild (Child-Pugh Class A) | No dose adjustment | No dose adjustment | No dose adjustment
Moderate (Child-Pugh Class B) | One tablet of tezacaftor 50 mg/ivacaftor 75 mg once daily | One tablet of tezacaftor 100 mg/ivacaftor 150 mg once daily | No ivacaftor dose
Severe (Child-Pugh Class C) | One tablet of tezacaftor 50 mg/ivacaftor 75 mg once daily (or less frequently) | One tablet of tezacaftor 100 mg/ivacaftor 150 mg once daily (or less frequently) | No ivacaftor dose

2.4 Dosage Adjustment for Patients Taking Drugs that are CYP3A Inhibitors

The dosing regimen of SYMDEKO should be adjusted when co-administered with moderate and strong CYP3A inhibitors.

Moderate CYP3A inhibitors:

When co-administered with moderate CYP3A inhibitors (e.g., fluconazole, erythromycin), the dosing regimen should be adjusted as in Table 3 [see Drug Interactions (7.2), Clinical Pharmacology (12.3), and Patient Counseling Information (17)].

Table 3: Dosing Schedule for Concomitant Use of SYMDEKO with Moderate CYP3A Inhibitors
 | Day 1 | Day 2 | Day 3 | Day 4 [Continue dosing with tezacaftor/ivacaftor or ivacaftor tablets on alternate days.]
Patients Aged 6 to <12 Years Weighing <30 kg
Morning
Tezacaftor 50 mg/ivacaftor 75 mg tablet | ✓ | - | ✓ | -
Ivacaftor 75 mg tablet | - | ✓ | - | ✓
Evening
Ivacaftor 75 mg tablet | - | - | - | -
Patients Aged 6 to <12 Years Weighing ≥30 kg and Patients Age ≥12 Years
Morning
Tezacaftor 100 mg/ivacaftor 150 mg tablet | ✓ | - | ✓ | -
Ivacaftor 150 mg tablet | - | ✓ | - | ✓
Evening
Ivacaftor 150 mg tablet | - | - | - | -

Strong CYP3A inhibitors:

When co-administered with strong CYP3A inhibitors (e.g., ketoconazole, itraconazole, posaconazole, voriconazole, telithromycin, and clarithromycin), the dosing regimen should be adjusted as in Table 4 [see Drug Interactions (7.2), Clinical Pharmacology (12.3), and Patient Counseling Information (17)].

Table 4: Dosing Schedule for Concomitant Use of SYMDEKO with Strong CYP3A Inhibitors
 | Day 1 | Day 2 and Day 3 | Day 4 [Continue dosing with tezacaftor/ivacaftor tablets twice a week, taken approximately 3 to 4 days apart.]
Patients Aged 6 to <12 Years Weighing <30 kg
Morning
Tezacaftor 50 mg/ivacaftor 75 mg tablet | ✓ | - | ✓
Evening [The evening dose of ivacaftor should not be taken on any day.]
Ivacaftor 75 mg tablet | - | - | -
Patients Aged 6 to <12 Years Weighing ≥30 kg and Patients Age ≥12 Years
Morning
Tezacaftor 100 mg/ivacaftor 150 mg tablet | ✓ | - | ✓
Evening
Ivacaftor 150 mg tablet | - | - | -

Food or drink containing grapefruit should be avoided during treatment with SYMDEKO [see Drug Interactions (7.2) and Patient Counseling Information (17)].

3 DOSAGE FORMS AND STRENGTHS

Tablets: Tezacaftor 50 mg/ivacaftor 75 mg fixed-dose combination tablets co-packaged with ivacaftor 75 mg tablets

- Tezacaftor 50 mg/ivacaftor 75 mg tablets are white, oblong-shaped, and debossed with "V50" on one side and plain on the other.
- Ivacaftor 75 mg tablets are light blue, oblong-shaped, and printed with "V 75" in black ink on one side and plain on the other.

Tablets: Tezacaftor 100 mg/ivacaftor 150 mg fixed-dose combination tablets co-packaged with ivacaftor 150 mg tablets

- Tezacaftor 100 mg/ivacaftor 150 mg tablets are yellow, oblong-shaped, and debossed with "V100" on one side and plain on the other.
- Ivacaftor 150 mg tablets are light blue, oblong-shaped, and printed with "V 150" in black ink on one side and plain on the other.

4 CONTRAINDICATIONS

None.

5 WARNINGS AND PRECAUTIONS

5.1 Transaminase (AST/ALT) Elevations

Elevated transaminases have been observed in patients with CF treated with SYMDEKO, as well as with ivacaftor monotherapy. Assessments of transaminases (ALT and AST) are recommended for all patients prior to initiating SYMDEKO, every 3 months during the first year of treatment, and annually thereafter. For patients with a history of transaminase elevations more frequent monitoring should be considered. In the event of significant elevations of transaminases, e.g., patients with ALT or AST >5 × upper limit of normal (ULN), or ALT or AST >3 × ULN with bilirubin >2 × ULN, dosing should be interrupted and laboratory tests closely followed until the abnormalities resolve. Following the resolution of transaminase elevations consider the benefits and risks of resuming treatment [see Adverse Reactions (6)].

5.2 Hypersensitivity Reactions, Including Anaphylaxis

Hypersensitivity reactions, including cases of anaphylaxis, have been reported in the postmarketing setting [see Adverse Reactions (6.2)]. If signs or symptoms of serious hypersensitivity reactions develop during treatment, discontinue SYMDEKO and institute appropriate therapy. Consider the benefits and risks for the individual patient to determine whether to resume treatment with SYMDEKO.

5.3 Intracranial Hypertension

Cases of intracranial hypertension (IH) have been reported in the postmarketing setting with the use of drugs containing the same or similar active ingredients as SYMDEKO [see Adverse Reactions (6.2)]. Clinical manifestations of IH include headache, blurred vision, diplopia, and potential vision loss; papilledema can be found on fundoscopy. If an unusual headache or visual disturbances occur during treatment, and IH is suspected, interrupt SYMDEKO and refer for prompt medical evaluation. Consider the benefits and risks for the individual patient to determine whether to resume treatment with SYMDEKO. Patients should be monitored until IH resolution and for recurrence. Patients with elevated vitamin A levels may be at increased risk.

5.4 Concomitant Use with CYP3A Inducers

Exposure to ivacaftor is significantly decreased and exposure to tezacaftor may be reduced by the concomitant use of CYP3A inducers, which may reduce the therapeutic effectiveness of SYMDEKO. Therefore, co-administration with strong CYP3A inducers is not recommended [see Drug Interactions (7.1), Clinical Pharmacology (12.3), and Patient Counseling Information (17)].

5.5 Cataracts

Cases of non-congenital lens opacities have been reported in pediatric patients treated with SYMDEKO, as well as with ivacaftor monotherapy. Although other risk factors were present in some cases (such as corticosteroid use, exposure to radiation), a possible risk attributable to treatment with SYMDEKO cannot be excluded. Baseline and follow-up ophthalmological examinations are recommended in pediatric patients initiating treatment with SYMDEKO [see Use in Specific Populations (8.4) and Patient Counseling Information (17)].

6 ADVERSE REACTIONS

The following adverse reactions are discussed in greater detail in other sections of the label:

- Transaminase Elevations [see Warnings and Precautions (5.1)]
- Hypersensitivity Reactions, Including Anaphylaxis [see Warnings and Precautions (5.2)]
- Intracranial Hypertension [see Warnings and Precautions (5.3)]
- Cataracts [see Warnings and Precautions (5.5)]

6.1 Clinical Trials Experience

Because clinical trials are conducted under widely varying conditions, adverse reaction rates observed in the clinical trials of a drug cannot be directly compared to rates in the clinical trials of another drug and may not reflect the rates observed in clinical practice.

The overall safety profile of SYMDEKO is based on data from 1001 patients in three double-blind, placebo-controlled, clinical trials: two parallel-group trials of 12 and 24-week duration and one cross-over design trial of 8 weeks duration. Eligible patients were also able to participate in an open-label extension safety study (up to 96 weeks of SYMDEKO). In the three placebo-controlled trials (Trials 1, 2, and 3), a total of 496 patients with CF aged 12 years and older received at least one dose of SYMDEKO. The proportion of patients who discontinued study drug prematurely due to adverse reactions was 1.6% for SYMDEKO-treated patients and 2.0% for placebo-treated patients. Serious adverse reactions, whether considered drug-related or not by the investigators, that occurred more frequently in SYMDEKO-treated patients compared to placebo included distal intestinal obstruction syndrome, 3 (0.6%) SYMDEKO-treated patients vs. 0 placebo. There were no deaths in the placebo-controlled trials, and one death in the open-label extension study due to respiratory failure and influenza infection in a patient who had discontinued SYMDEKO seven weeks prior.

The safety profile of SYMDEKO was generally similar across all subgroups of patients, including analysis by age, sex, baseline percent predicted FEV1 (ppFEV1), and geographic regions.

Table 5 shows adverse reactions occurring in ≥3% of SYMDEKO-treated patients that also occurred at a higher rate than in the placebo-treated patients in the 12- and 24-week placebo-controlled, parallel-group trials (Trials 1 and 3).

Table 5: Incidence of Adverse Drug Reactions in ≥3% of SYMDEKO-Treated Patients and Greater than Placebo
Adverse Reactions (Preferred Term) | SYMDEKO N=334 n (%) | Placebo N=343 n (%)
Headache | 49 (15) | 44 (13)
Nausea | 29 (9) | 24 (7)
Sinus congestion | 13 (4) | 6 (2)
Dizziness | 12 (4) | 8 (2)

The safety data from the following trials are similar to that observed in Trials 1 and 3:

- an 8-week randomized, double-blind, placebo-controlled crossover study in 244 patients with CF aged 12 years and older who were heterozygous for the F508del mutation and a second mutation predicted to be responsive to tezacaftor/ivacaftor (Trial 2).
- a 24-week open-label study in 70 patients with CF aged 6 to less than 12 years who were either homozygous for the F508del mutation or heterozygous for the F508del mutation and a second mutation predicted to be responsive to tezacaftor/ivacaftor (Trial 4).

Laboratory Abnormalities

Transaminase elevations

During the placebo-controlled trials in patients aged 12 years and older, the incidence of maximum transaminase (ALT or AST) >8, >5, and >3 × the upper limit of normal (ULN) was similar between SYMDEKO-treated patients and placebo-treated patients; 0.2%, 1.0%, and 3.4% in SYMDEKO-treated patients, and 0.4%, 1.0%, and 3.4% in placebo-treated patients. One patient (0.2%) on SYMDEKO and 2 patients (0.4%) on placebo permanently discontinued treatment for elevated transaminases. No SYMDEKO-treated patients experienced a transaminase elevation >3 × ULN associated with elevated total bilirubin >2 × ULN.

During the 24-week, open-label study in patients aged 6 to less than 12 years (Trial 4), the incidence of maximum transaminase (ALT or AST) >8, >5, and >3 × ULN were 1.4%, 4.3%, and 10.0%, respectively. No SYMDEKO-treated patients experienced a transaminase elevation >3 × ULN associated with elevated total bilirubin >2 × ULN or discontinued SYMDEKO treatment due to transaminase elevations.

6.2 Postmarketing Experience

Postmarketing Adverse Reactions with SYMDEKO

The following adverse reactions have been identified during post approval use of SYMDEKO. Because these reactions are reported voluntarily from a population of uncertain size, it is not always possible to reliably estimate their frequency or establish a causal relationship to drug exposure.

Immune System Disorders: anaphylaxis

Skin: rash

Postmarketing Adverse Reactions with Other Drugs Containing the Same or Similar Active Ingredients as SYMDEKO

The following adverse reactions have been identified during post approval use of drugs containing the same or similar active ingredients as SYMDEKO. Because these reactions are reported voluntarily from a population of uncertain size, it is not always possible to reliably estimate their frequency or establish a causal relationship to drug exposure.

Nervous System Disorders: intracranial hypertension

7 DRUG INTERACTIONS

Potential for other drugs to affect tezacaftor/ivacaftor

7.1 Inducers of CYP3A

Tezacaftor and ivacaftor are substrates of CYP3A (ivacaftor is a sensitive substrate of CYP3A). Concomitant use of CYP3A inducers may result in reduced exposures and thus reduced SYMDEKO efficacy. Co-administration of ivacaftor with rifampin, a strong CYP3A inducer, significantly decreased ivacaftor exposure (area under the curve [AUC]) by 89%. Tezacaftor exposures can also be expected to decrease significantly during co-administration with strong CYP3A inducers. Therefore, co-administration of SYMDEKO with strong CYP3A inducers is not recommended [see Warnings and Precautions (5.4), Clinical Pharmacology (12.3), and Patient Counseling Information (17)].

Examples of strong CYP3A inducers include:

- rifampin, rifabutin, phenobarbital, carbamazepine, phenytoin, and St. John's wort (Hypericum perforatum)

7.2 Inhibitors of CYP3A

Co-administration with itraconazole, a strong CYP3A inhibitor, increased tezacaftor exposure (AUC) by 4.0-fold and ivacaftor by 15.6-fold. When co-administered with strong CYP3A inhibitors, the dosing regimen of SYMDEKO should be adjusted [see Dosage and Administration (2.4), Clinical Pharmacology (12.3), and Patient Counseling Information (17)].

Examples of strong CYP3A inhibitors include:

- ketoconazole, itraconazole, posaconazole, and voriconazole
- telithromycin and clarithromycin

Co-administration of fluconazole increased ivacaftor exposure (AUC) by 3.0-fold. Simulation suggested co-administration with fluconazole, a moderate CYP3A inhibitor, may increase tezacaftor exposure (AUC) by approximately 2.0-fold. When co-administered with moderate CYP3A inhibitors, the dosing regimen of SYMDEKO should be adjusted [see Dosage and Administration (2.4), Clinical Pharmacology (12.3), and Patient Counseling Information (17)].

Examples of moderate CYP3A inhibitors include:

- fluconazole
- erythromycin

Co-administration of SYMDEKO with grapefruit juice, which contains one or more components that moderately inhibit CYP3A, may increase exposure of tezacaftor and ivacaftor; therefore, food or drink containing grapefruit should be avoided during treatment with SYMDEKO [see Dosage and Administration (2.4), Clinical Pharmacology (12.3), and Patient Counseling Information (17)].

7.3 Ciprofloxacin

Co-administration of SYMDEKO with ciprofloxacin had no significant effect on the exposure of tezacaftor or ivacaftor. Therefore, no dosage adjustment is necessary during concomitant administration of SYMDEKO with ciprofloxacin [see Clinical Pharmacology (12.3)].

Potential for tezacaftor/ivacaftor to affect other drugs

7.4 CYP3A Substrates

Co-administration of SYMDEKO with midazolam (oral), a sensitive CYP3A substrate, did not affect midazolam exposure. No dosage adjustment of CYP3A substrates is required when co-administered with SYMDEKO [see Clinical Pharmacology (12.3)].

7.5 CYP2C9 Substrates

Ivacaftor may inhibit CYP2C9; therefore, monitoring of the international normalized ratio (INR) during co-administration of SYMDEKO with warfarin is recommended. Other medicinal products for which exposure may be increased by SYMDEKO include glimepiride and glipizide; these medicinal products should be used with caution [see Clinical Pharmacology (12.3)].

7.6 Digoxin and Other P-gp Substrates

Co-administration of SYMDEKO with digoxin, a sensitive P-gp substrate, increased digoxin exposure by 1.3-fold consistent with weak inhibition of P-gp by ivacaftor. Administration of SYMDEKO may increase systemic exposure of medicinal products that are sensitive substrates of P-gp, which may increase or prolong their therapeutic effect and adverse reactions. When used concomitantly with digoxin or other substrates of P-gp with a narrow therapeutic index such as cyclosporine, everolimus, sirolimus, and tacrolimus, caution and appropriate monitoring should be used [see Clinical Pharmacology (12.3)].

7.7 Hormonal Contraceptives

SYMDEKO has been studied with an ethinyl estradiol/norethindrone oral contraceptive and was found to have no significant effect on the exposures of the hormonal contraceptive. SYMDEKO is not expected to modify the efficacy of hormonal contraceptives [see Clinical Pharmacology (12.3)].

8 USE IN SPECIFIC POPULATIONS

8.1 Pregnancy

Risk Summary

There are limited and incomplete human data from clinical trials and postmarketing reports on the use of SYMDEKO or its individual components, tezacaftor and ivacaftor, in pregnant women to inform a drug-associated risk. Although there are no animal reproduction studies with the concomitant administration of tezacaftor and ivacaftor, separate reproductive and developmental studies were conducted with tezacaftor and ivacaftor in pregnant rats and rabbits. In animal reproduction studies, oral administration of tezacaftor to pregnant rats and rabbits during organogenesis demonstrated no teratogenicity or adverse developmental effects at doses that produced maternal exposures up to approximately 3 times the exposure at the maximum recommended human dose (MRHD) in rats and 0.2 times the MRHD in rabbits (based on summed AUCs for tezacaftor and M1 metabolite). Oral administration of ivacaftor to pregnant rats and rabbits during organogenesis demonstrated no teratogenicity or adverse developmental effects at doses that produced maternal exposures up to approximately 6 and 16 times the exposure at the MRHD, respectively. No adverse developmental effects were observed after oral administration of either tezacaftor or ivacaftor to pregnant rats from the period of organogenesis through lactation at doses that produced maternal exposures approximately 1 and 4 times the exposures at the MRHD, respectively (see Data).

The background risk of major birth defects and miscarriage for the indicated population is unknown. In the U.S. general population, the estimated background risk of major birth defects and miscarriage in clinically recognized pregnancies is 2% to 4% and 15% to 20%, respectively.

Data

Animal Data

Tezacaftor

In an embryo-fetal development study in pregnant rats dosed during the period of organogenesis from gestation Days 6-17, tezacaftor was not teratogenic and did not affect fetal development or survival at exposures up to 3 times the MRHD (based on summed AUCs for tezacaftor and M1 metabolite at maternal oral doses up to 100 mg/kg/day). In an embryo-fetal development study in pregnant rabbits dosed during the period of organogenesis from gestation Days 7-20, tezacaftor was not teratogenic and did not affect fetal development or survival at exposures up to 0.2 times the MRHD (based on summed AUCs for tezacaftor and M1 metabolite at maternal oral doses up to 25 mg/kg/day). Lower fetal body weights were observed in rabbits at a maternally toxic dose that produced exposures approximately 1 times the MRHD (at a maternal dose of 50 mg/kg/day). In a pre- and postnatal development (PPND) study in pregnant rats dosed from gestation Day 6 through lactation Day 18, tezacaftor had no adverse developmental effects on pups at an exposure of approximately 1 times the MRHD (based on summed AUCs for tezacaftor and M1 metabolite at a maternal dose of 25 mg/kg/day). Decreased fetal body weights and early developmental delays in pinna detachment, eye opening, and righting reflex occurred at a maternally toxic dose (based on maternal weight loss) that produced exposures approximately 2 times the exposure at the MRHD (based on summed AUCs for tezacaftor and M1 metabolite at a maternal oral dose of 50 mg/kg/day). Placental transfer of tezacaftor was observed in pregnant rats.

Ivacaftor

In an embryo-fetal development study in pregnant rats dosed during the period of organogenesis from gestation Days 7-17, ivacaftor was not teratogenic and did not affect fetal survival at exposures up to 6 times the MRHD (based on summed AUCs for ivacaftor and its metabolites at a maternal oral dose of 200 mg/kg/day). In an embryo-fetal development study in pregnant rabbits dosed during the period of organogenesis from gestation Days 7-19, ivacaftor was not teratogenic and did not affect fetal development or survival at exposures up to 16 times the MRHD (on an ivacaftor AUC basis at maternal oral doses up to 100 mg/kg/day). In a PPND study in pregnant rats dosed from gestation Day 7 through lactation Day 20, ivacaftor had no effects on delivery or growth and development of offspring at exposures up to 4 times the MRHD (based on summed AUCs for ivacaftor and its metabolites at maternal oral doses up to 100 mg/kg/day). Decreased fetal body weights were observed at a maternally toxic dose that produced exposures 6 times the MRHD. Placental transfer of ivacaftor was observed in pregnant rats and rabbits.

8.2 Lactation

Risk Summary

There is no information regarding the presence of tezacaftor or ivacaftor in human milk, the effects on the breastfed infant, or the effects on milk production. Both tezacaftor and ivacaftor are excreted into the milk of lactating rats (see Data). The developmental and health benefits of breastfeeding should be considered along with the mother's clinical need for SYMDEKO and any potential adverse effects on the breastfed child from SYMDEKO or from the underlying maternal condition.

Data

Tezacaftor

Lacteal excretion of tezacaftor in rats was demonstrated following a single oral dose (30 mg/kg) of ^14C-tezacaftor administered 6 to 10 days postpartum to lactating dams. Exposure of ^14C-tezacaftor in milk was approximately 3 times higher than in plasma (based on AUC0-72h).

Ivacaftor

Lacteal excretion of ivacaftor in rats was demonstrated following a single oral dose (100 mg/kg) of ^14C-ivacaftor administered 9 to 10 days postpartum to lactating dams. Exposure of ^14C-ivacaftor in milk was approximately 1.5 times higher than in plasma (based on AUC0-24h).

8.4 Pediatric Use

The safety and effectiveness of SYMDEKO for the treatment of CF have been established in pediatric patients aged 6 to less than 18 years who are homozygous for the F508del mutation or who have at least one mutation in the CFTR gene that is responsive to tezacaftor/ivacaftor based on in vitro data and/or clinical evidence [see Clinical Pharmacology (12.1) and Clinical Studies (14)].

Clinical trials included the following patients with CF:

- 12 to less than 18 years of age who are homozygous for the F508del mutation [see Adverse Reactions (6) and Clinical Studies (14)].
- 12 to less than 18 years of age who are heterozygous for the F508del mutation and a second mutation predicted to be responsive to tezacaftor/ivacaftor [see Adverse Reactions (6) and Clinical Studies (14)].
- 6 to less than 12 years of age who are either homozygous for the F508del mutation or heterozygous for the F508del mutation and a second mutation predicted to be responsive to tezacaftor/ivacaftor [see Adverse Reactions (6) and Clinical Pharmacology (12)].

The effectiveness of SYMDEKO in patients aged 6 to less than 12 years was extrapolated from patients aged 12 years and older with support from population pharmacokinetic analyses showing similar tezacaftor and ivacaftor exposure levels in patients aged 6 to less than 12 years and in patients aged 12 years and older [see Clinical Pharmacology (12.3)]. Safety of SYMDEKO in this population was derived from a 24-week, open-label, clinical trial in 70 patients aged 6 to less than 12 years (mean age at screening 8.1 years) administered either tezacaftor 50 mg/ivacaftor 75 mg and ivacaftor 75 mg or tezacaftor 100 mg/ivacaftor 150 mg and ivacaftor 150 mg, 12 hours apart (Trial 4). The safety profile for patients in this trial was similar to that observed in Trials 1 and 3 [see Adverse Reactions (6.1)].

The safety and effectiveness of SYMDEKO in patients with CF younger than 6 years of age have not been studied.

Juvenile Animal Toxicity Data

Findings of cataracts were observed in juvenile rats dosed from postnatal Day 7 through 35 with ivacaftor dose levels of 10 mg/kg/day and higher (0.25 times the MRHD based on systemic exposure of ivacaftor and its metabolites). This finding has not been observed in older animals.

8.5 Geriatric Use

Clinical trials of SYMDEKO did not include sufficient numbers of patients 65 years of age and over to determine whether they respond differently from younger patients.

8.6 Hepatic Impairment

No dosage adjustment is necessary for patients with mild hepatic impairment (Child-Pugh Class A). A reduced dosage of SYMDEKO is recommended in patients with moderate hepatic impairment (Child-Pugh Class B). There is no experience in patients with severe hepatic impairment (Child-Pugh Class C), but tezacaftor/ivacaftor exposure is expected to be higher than in patients with moderate hepatic impairment. Therefore, use with caution at a reduced dosage in patients with severe hepatic impairment after weighing the risks and benefits of treatment [see Dosage and Administration (2.3), Clinical Pharmacology (12.3), and Patient Counseling Information (17)].

8.7 Renal Impairment

SYMDEKO has not been studied in patients with moderate or severe renal impairment or in patients with end-stage renal disease. No dosage adjustment is recommended for mild and moderate renal impairment. Caution is recommended in patients with severe renal impairment or end-stage renal disease [Clinical Pharmacology (12.3)].

8.8 Patients with Severe Lung Dysfunction

Trial 1 and Trial 2 included a total of 39 SYMDEKO-treated patients with ppFEV1 <40 at baseline (range: 30-40); 23 patients in Trial 1 and 16 patients in Trial 2. There were 24 placebo-treated patients in Trial 1, and 15 placebo- and 13 ivacaftor-treated patients in Trial 2, with ppFEV1 <40 at baseline. The safety and efficacy in this subgroup were comparable to the overall results observed in both Trials 1 and 2.

10 OVERDOSAGE

No specific antidote is available for overdose with SYMDEKO. Treatment of overdosage consists of general supportive measures including monitoring of vital signs and observation of the clinical status of the patient.

11 DESCRIPTION

SYMDEKO is co-packaged as a tezacaftor/ivacaftor fixed-dose combination tablet and an ivacaftor tablet. Both tablets are for oral administration.

Tezacaftor 50 mg/ivacaftor 75 mg fixed-dose combination tablets and ivacaftor 75 mg tablets:

The tezacaftor/ivacaftor fixed-dose combination tablet is available as a white, oblong-shaped, film-coated tablet containing 50 mg of tezacaftor, 75 mg of ivacaftor, and the following inactive ingredients: croscarmellose sodium, hypromellose, hypromellose acetate succinate, magnesium stearate, microcrystalline cellulose and sodium lauryl sulfate. The tablet film coat contains HPMC/hypromellose 2910, hydroxypropyl cellulose, talc and titanium dioxide.

The ivacaftor tablet is available as a light blue, oblong-shaped, film-coated tablet containing 75 mg of ivacaftor and the following inactive ingredients: colloidal silicon dioxide, croscarmellose sodium, hypromellose acetate succinate, lactose monohydrate, magnesium stearate, microcrystalline cellulose, and sodium lauryl sulfate. The tablet film coat contains carnauba wax, FD&C Blue #2, PEG 3350, polyvinyl alcohol, talc, and titanium dioxide. The printing ink contains ammonium hydroxide, iron oxide black, propylene glycol, and shellac.

Tezacaftor 100 mg/ivacaftor 150 mg fixed-dose combination tablets and ivacaftor 150 mg tablets:

The tezacaftor/ivacaftor fixed-dose combination tablet is available as a yellow, oblong-shaped, film-coated tablet containing 100 mg of tezacaftor, 150 mg of ivacaftor, and the following inactive ingredients: croscarmellose sodium, hypromellose, hypromellose acetate succinate, magnesium stearate, microcrystalline cellulose and sodium lauryl sulfate. The tablet film coat contains HPMC/hypromellose 2910, hydroxypropyl cellulose, iron oxide yellow, talc and titanium dioxide.

The ivacaftor tablet is available as a light blue, oblong-shaped, film-coated tablet containing 150 mg of ivacaftor and the following inactive ingredients: colloidal silicon dioxide, croscarmellose sodium, hypromellose acetate succinate, lactose monohydrate, magnesium stearate, microcrystalline cellulose, and sodium lauryl sulfate. The tablet film coat contains carnauba wax, FD&C Blue #2, PEG 3350, polyvinyl alcohol, talc, and titanium dioxide. The printing ink contains ammonium hydroxide, iron oxide black, propylene glycol, and shellac.

The active ingredients of SYMDEKO are described below.

Tezacaftor

Tezacaftor is a white to off-white powder that is practically insoluble in water (<5 microgram/mL). Its chemical name of tezacaftor is 1-(2,2-difluoro-2H-1,3-benzodioxol-5-yl)-N-{1-[(2R)-2,3-dihydroxypropyl]-6-fluoro-2-(1-hydroxy-2-methylpropan-2-yl)-1Hindol-5-yl}cyclopropane-1-carboxamide. Its molecular formula is C26H27N2F3O6 and its molecular weight is 520.50. Tezacaftor has the following structural formula:

Ivacaftor

Ivacaftor is a white to off-white powder that is practically insoluble in water (<0.05 microgram/mL). Pharmacologically it is a CFTR potentiator. Its chemical name is N-(2,4-di-tert-butyl-5-hydroxyphenyl)-1,4-dihydro-4-oxoquinoline-3-carboxamide. Its molecular formula is C24H28N2O3 and its molecular weight is 392.49. Ivacaftor has the following structural formula:

12 CLINICAL PHARMACOLOGY

12.1 Mechanism of Action

Tezacaftor facilitates the cellular processing and trafficking of select mutant forms of CFTR (including F508del-CFTR) to increase the amount of mature CFTR protein delivered to the cell surface. Ivacaftor is a CFTR potentiator that facilitates increased chloride transport by potentiating the channel-open probability (or gating) of the CFTR protein at the cell surface. For ivacaftor to function CFTR protein must be present at the cell surface. Ivacaftor can potentiate the CFTR protein delivered to the cell surface by tezacaftor, leading to a further enhancement of chloride transport than either agent alone. The combined effect of tezacaftor and ivacaftor is increased quantity and function of CFTR at the cell surface, resulting in increases in chloride transport.

CFTR Chloride Transport Assay in Fischer Rat Thyroid (FRT) cells expressing mutant CFTR

The chloride transport response of mutant CFTR protein to tezacaftor/ivacaftor was determined in Ussing chamber electrophysiology studies using a panel of FRT cell lines transfected with individual CFTR mutations. Tezacaftor/ivacaftor increased chloride transport in FRT cells expressing CFTR mutations that result in CFTR protein being delivered to the cell surface.

The in vitro chloride transport response threshold was designated as a net increase of at least 10% of normal over baseline because it is predictive or reasonably expected to predict clinical benefit. For individual mutations, the magnitude of the net change over baseline in CFTR-mediated chloride transport in vitro is not correlated with the magnitude of clinical response.

Note that splice site mutations cannot be studied in the FRT assay.

Table 6 lists responsive CFTR mutations based on (1) a clinical FEV1 response and/or (2) in vitro data in FRT cells, indicating that tezacaftor/ivacaftor increases chloride transport to at least 10% of normal over baseline. CFTR gene mutations that are not responsive to ivacaftor alone are not expected to respond to SYMDEKO except for F508del homozygotes.

Table 6: List of CFTR Gene Mutations that Produce CFTR Protein and are Responsive to SYMDEKO
546insCTA | E92K | G576A | L346P | R117G | S589N
711+3A→G [Clinical data for these mutations in Clinical Studies [see Clinical Studies (14.1 and 14.2)].] | E116K | G576A;R668C [Complex/compound mutations where a single allele of the CFTR gene has multiple mutations; these exist independent of the presence of mutations on the other allele.] | L967S | R117H | S737F
2789+5G→A | E193K | G622D | L997F | R117L | S912L
3272-26A→G | E403D | G970D | L1324P | R117P | S945L
3849+10kbC→T | E588V | G1069R | L1335P | R170H | S977F
A120T | E822K | G1244E | L1480P | R258G | S1159F
A234D | E831X | G1249R | M152V | R334L | S1159P
A349V | F191V | G1349D | M265R | R334Q | S1251N
A455E | F311del | H939R | M952I | R347H | S1255P
A554E | F311L | H1054D | M952T | R347L | T338I
A1006E | F508C | H1375P | P5L | R347P | T1036N
A1067T | F508C;S1251N | I148T | P67L | R352Q | T1053I
D110E | F508del [A patient must have two copies of the F508del mutation or at least one copy of a responsive mutation presented in Table 6 to be indicated.] | I175V | P205S | R352W | V201M
D110H | F575Y | I336K | Q98R | R553Q | V232D
D192G | F1016S | I601F | Q237E | R668C | V562I
D443Y | F1052V | I618T | Q237H | R751L | V754M
D443Y;G576A;R668C | F1074L | I807M | Q359R | R792G | V1153E
D579G | F1099L | I980K | Q1291R | R933G | V1240G
D614G | G126D | I1027T | R31L | R1066H | V1293G
D836Y | G178E | I1139V | R74Q | R1070Q | W1282R
D924N | G178R | I1269N | R74W | R1070W | Y109N
D979V | G194R | I1366N | R74W;D1270N | R1162L | Y161S
D1152H | G194V | K1060T | R74W;V201M | R1283M | Y1014C
D1270N | G314E | L15P | R74W;V201M;D1270N | R1283S | Y1032C
E56K | G551D | L206W | R75Q | S549N
E60K | G551S | L320V | R117C | S549R

12.2 Pharmacodynamics

Effects on Sweat Chloride

In Trial 1 (patients aged 12 years and older who were homozygous for the F508del mutation), the treatment difference between SYMDEKO and placebo in mean absolute change from baseline in sweat chloride through Week 24 was -10.1 mmol/L (95% CI: -11.4, -8.8).

In Trial 2 (patients aged 12 years and older who were heterozygous for the F508del mutation and a second mutation predicted to be responsive to tezacaftor/ivacaftor), the treatment difference in mean absolute change from baseline in sweat chloride through Week 8 was -9.5 mmol/L (95% CI: -11.7, -7.3) between SYMDEKO and placebo, and -4.5 mmol/L (95% CI: -6.7, -2.3) between ivacaftor and placebo.

In Trial 4 (patients aged 6 to less than 12 years) a reduction in sweat chloride was observed from baseline through Week 4 and sustained throughout the 24-week treatment period. Mean absolute change in sweat chloride from baseline through Week 24 was -14.5 mmol/L (95% CI: -17.4, -11.6).

Cardiac Electrophysiology

At a dose 3 times the maximum approved recommended dose, tezacaftor does not prolong the QT interval to any clinically relevant extent.

In a separate study of ivacaftor evaluating doses up to 3 times the maximum approved recommended dose, ivacaftor does not prolong the QT interval to any clinically relevant extent.

12.3 Pharmacokinetics

The pharmacokinetics of tezacaftor and ivacaftor are similar between healthy adult volunteers and patients with CF. Following once-daily dosing of tezacaftor and twice-daily dosing of ivacaftor in patients with CF, plasma concentrations of tezacaftor and ivacaftor reach steady-state within 8 days and within 3 to 5 days, respectively, after starting treatment. At steady-state, the accumulation ratio is approximately 1.5 for tezacaftor and 2.2 for ivacaftor. Exposures of tezacaftor (administered alone or in combination with ivacaftor) increase in an approximately dose-proportional manner with increasing doses from 10 mg to 300 mg once daily.

Key pharmacokinetic parameters for tezacaftor and ivacaftor at steady state are shown in Table 7.

Table 7: Mean (SD) Pharmacokinetic Parameters of Tezacaftor and Ivacaftor at Steady State in Patients with CF
 | Drug | Cmax (mcg/mL) | Effective t½ (h) | AUC0-24h or AUC0-12h (mcg∙h/mL) [AUC0-24h for tezacaftor and AUC0-12h for ivacaftor]
Tezacaftor 100 mg once daily/ivacaftor 150 mg every 12 hours | Tezacaftor | 5.95 (1.50) | 15.0 (3.44) | 84.5 (27.8)
Tezacaftor 100 mg once daily/ivacaftor 150 mg every 12 hours | Ivacaftor | 1.17 (0.424) | 13.7 (6.06) | 11.3 (4.60)

Absorption

After a single dose in healthy subjects in the fed state, tezacaftor was absorbed with a median (range) time to maximum concentration (tmax) of approximately 4 hours (2 to 6 hours). The median (range) tmax of ivacaftor was approximately 6 hours (3 to 10 hours) in the fed state.

When a single dose of tezacaftor/ivacaftor was administered with fat-containing foods, tezacaftor exposure was similar and ivacaftor exposure was approximately 3 times higher than when taken in a fasting state.

Distribution

Tezacaftor is approximately 99% bound to plasma proteins, primarily to albumin. Ivacaftor is approximately 99% bound to plasma proteins, primarily to alpha 1-acid glycoprotein and albumin. After oral administration of tezacaftor 100 mg once daily/ivacaftor 150 mg every 12 hours in patients with CF in the fed state, the mean (±SD) for apparent volume of distribution of tezacaftor and ivacaftor was 271 (157) L and 206 (82.9) L, respectively. Neither tezacaftor nor ivacaftor partition preferentially into human red blood cells.

Elimination

After oral administration of tezacaftor 100 mg once daily/ivacaftor 150 mg every 12 hours in patients with CF in the fed state, the mean (±SD) for apparent clearance values of tezacaftor and ivacaftor were 1.31 (0.41) and 15.7 (6.38) L/h, respectively. After steady-state dosing of tezacaftor in combination with ivacaftor in patients with CF, the effective half-lives of tezacaftor and ivacaftor were approximately 15 (3.44) and 13.7 (6.06) hours, respectively.

Metabolism

Tezacaftor is metabolized extensively in humans. In vitro data suggested that tezacaftor is metabolized mainly by CYP3A4 and CYP3A5. Following oral administration of a single dose of 100 mg ^14C-tezacaftor to healthy male subjects, M1, M2, and M5 were the three major circulating metabolites of tezacaftor in humans. M1 has the similar potency to that of tezacaftor and is considered pharmacologically active. M2 is much less pharmacologically active than tezacaftor or M1, and M5 is not considered pharmacologically active. Another minor circulating metabolite, M3, is formed by direct glucuronidation of tezacaftor.

Ivacaftor is also metabolized extensively in humans. In vitro and in vivo data indicate that ivacaftor is metabolized primarily by CYP3A4 and CYP3A5. M1 and M6 are the two major metabolites of ivacaftor in humans. M1 has approximately one-sixth the potency of ivacaftor and is considered pharmacologically active. M6 is not considered pharmacologically active.

Excretion

Following oral administration of ^14C-tezacaftor, the majority of the dose (72%) was excreted in the feces (unchanged or as the M2 metabolite) and about 14% was recovered in urine (mostly as M2 metabolite), resulting in a mean overall recovery of 86% up to 21 days after the dose. Less than 1% of the administrated dose was excreted in urine as unchanged tezacaftor, showing that renal excretion is not the major pathway of tezacaftor elimination in humans.

Following oral administration of ivacaftor alone, the majority of ivacaftor (87.8%) is eliminated in the feces after metabolic conversion. There was minimal elimination of ivacaftor and its metabolites in urine (only 6.6% of total radioactivity was recovered in the urine), and there was negligible urinary excretion of ivacaftor as unchanged drug.

Specific Populations

Based on population PK analyses, the PK exposure parameters of tezacaftor/ivacaftor in children and adolescents (ages 6 to <18 years) are similar to the AUCss range observed in adults when given in combination.

Pediatric patients aged 6 to less than 12 years

Table 8: Tezacaftor/Ivacaftor Exposure by Age Group, Mean (SD)
Age Group | Dose | Tezacaftor AUCss mcg∙h/mL [AUC 0-24h for tezacaftor and AUC 0-12h for ivacaftor] | Ivacaftor AUCss mcg∙h/mL
6 to <12 years [Exposures in ≥30 kg weight range are predictions derived from the population PK model] |  | 71.3 (28.3) | 8.5 (3.34)
6 to <12 years (<30 kg) | tezacaftor 50 mg/ivacaftor 75 mg | 56.7 (22.3) | 6.92 (2.07)
6 to <12 years (≥30 kg) | tezacaftor 100 mg/ivacaftor 150 mg | 92.7 (21.9) | 10.8 (3.52)

Pediatric patients aged 12 to less than 18 years

Following oral administration of SYMDEKO tablets, tezacaftor 100 mg once daily/ivacaftor 150 mg every 12 hours, the mean (±SD) AUCss for tezacaftor and ivacaftor was 97.1 (35.8) mcg∙h/mL and 11.4 (5.50) mcg∙h/mL, respectively, similar to the mean AUCss in adult patients administered SYMDEKO tablets, tezacaftor 100 mg once daily/ivacaftor 150 mg every 12 hours.

Patients with Hepatic Impairment

Following multiple doses of tezacaftor and ivacaftor for 10 days, patients with moderately impaired hepatic function (Child-Pugh Class B, score 7-9) had an approximately 36% increase in AUC and a 10% increase in Cmax for tezacaftor, and a 1.5-fold increase in ivacaftor AUC compared with healthy subjects matched for demographics. In a separate study, patients with moderately impaired hepatic function (Child-Pugh Class B, score 7-9) had similar ivacaftor Cmax, but an approximately 2.0-fold increase in ivacaftor AUC0-∞ compared with healthy subjects matched for demographics.

Pharmacokinetic studies have not been conducted in patients with mild (Child-Pugh Class A, score 5-6) or severe hepatic impairment (Child-Pugh Class C, score 10-15) receiving SYMDEKO. The magnitude of increase in exposure in patients with severe hepatic impairment is unknown but is expected to be higher than that observed in patients with moderate hepatic impairment [see Dosage and Administration (2.3), Use in Specific Populations (8.6), and Patient Counseling Information (17)].

Patients with Renal Impairment

SYMDEKO has not been studied in patients with moderate or severe renal impairment (creatinine clearance ≤30 mL/min) or in patients with end-stage renal disease. In a human pharmacokinetic study with tezacaftor alone, there was minimal elimination of tezacaftor and its metabolites in urine (only 13.7% of total radioactivity was recovered in the urine with 0.79% as unchanged drug).

In a human pharmacokinetic study with ivacaftor alone, there was minimal elimination of ivacaftor and its metabolites in urine (only 6.6% of total radioactivity was recovered in the urine).

In population pharmacokinetic analysis, data from 665 patients on tezacaftor or tezacaftor in combination with ivacaftor in clinical trials indicated that mild renal impairment (N=147; eGFR 60 to less than 90 mL/min/1.73 m^2) and moderate renal impairment (N=7; eGFR 30 to less than 60 mL/min/1.73 m^2) did not affect the clearance of tezacaftor significantly [see Use in Specific Populations (8.7)].

Male and Female Patients

The pharmacokinetic parameters of tezacaftor and ivacaftor are similar in males and females.

Drug Interactions Studies

Drug interaction studies were performed with SYMDEKO and other drugs likely to be co-administered or drugs commonly used as probes for pharmacokinetic interaction studies [see Drug Interactions (7)].

Potential for Tezacaftor/Ivacaftor to Affect Other Drugs

Clinical studies (with rosiglitazone and desipramine – see Table 9) showed that ivacaftor is not an inhibitor of CYP2C8 or CYP2D6. Based on in vitro results, ivacaftor has the potential to inhibit CYP3A and P-gp, and may also inhibit CYP2C9. In vitro, ivacaftor was not an inducer of CYP isozymes. Ivacaftor is not an inhibitor of transporters OATP1B1, OATP1B3, OCT1, OCT2, OAT1, or OAT3.

Based on in vitro results, tezacaftor has a low potential to inhibit CYP1A2, CYP2B6, CYP2C8, CYP2C9, CYP2C19, CYP2D6, and CYP3A4. Tezacaftor has a low potential to induce CYP3A, but it is not an inducer of CYP1A2 and CYP2B6. Tezacaftor has a low potential to inhibit transporters P-gp, BCRP, OATP1B3, OCT2, OAT1, or OAT3.

Clinical studies with midazolam showed that SYMDEKO is not an inhibitor of CYP3A. Co-administration of SYMDEKO with digoxin, a sensitive P-gp substrate, increased digoxin exposure by 1.3-fold. Co-administration of SYMDEKO with an ethinyl estradiol/ norethindrone oral contraceptive had no significant effect on the exposures of the hormonal contraceptives. Co-administration of SYMDEKO with pitavastatin, an OATP1B1 substrate, had no clinically relevant effect on the exposure of pitavastatin.

The effects of tezacaftor and ivacaftor (or ivacaftor alone) on the exposure of co-administered drugs are shown in Table 9 [see Drug Interactions (7)].

Potential for Other Drugs to Affect Tezacaftor/Ivacaftor

In vitro studies showed that ivacaftor and tezacaftor were substrates of CYP3A enzymes (i.e., CYP3A4 and CYP3A5). Exposure to ivacaftor and tezacaftor will be reduced by concomitant CYP3A inducers and increased by concomitant CYP3A inhibitors.

In vitro studies showed that tezacaftor is a substrate for the uptake transporter OATP1B1, and efflux transporters P-gp and BCRP. Tezacaftor is not a substrate for OATP1B3. In vitro studies showed that ivacaftor is not a substrate for OATP1B1, OATP1B3, or P-gp.

The effects of co-administered drugs on the exposure of tezacaftor and ivacaftor (or ivacaftor alone) are shown in Table 10 [see Dosage and Administration (2.4) and Drug Interactions (7)].

Table 9: Impact of Tezacaftor/Ivacaftor or Ivacaftor on Other Drugs
 | Dose and Schedule |  |  | Mean Ratio (90% CI) of Other Drugs No Effect=1.0
Drug | Dose | TEZ/IVA or IVA | Effect on Drug PK | AUC | Cmax
Midazolam | 2 mg single oral dose | TEZ 100 mg/IVA 150 mg every morning + IVA 150 mg every evening | ↔ Midazolam | 1.12 (1.01, 1.25) | 1.13 (1.01, 1.25)
Digoxin | 0.5 mg single dose | TEZ 100 mg/IVA 150 mg every morning + IVA 150 mg every evening | ↑ Digoxin | 1.30 (1.17, 1.45) | 1.32 (1.07, 1.64)
Oral Contraceptive | Ethinyl estradiol/ Norethindrone 0.035 mg/1.0 mg once daily | TEZ 100 mg/IVA 150 mg every morning + IVA 150 mg every evening | ↔ Ethinyl estradiol | 1.12 (1.03, 1.22) | 1.15 (0.99, 1.33)
Oral Contraceptive | Ethinyl estradiol/ Norethindrone 0.035 mg/1.0 mg once daily | TEZ 100 mg/IVA 150 mg every morning + IVA 150 mg every evening | ↔ Norethindrone | 1.05 (0.98, 1.12) | 1.01 (0.87, 1.19)
Pitavastatin | 2 mg single dose | TEZ 100 mg/IVA 150 mg every morning + IVA 150 mg every evening | ↑ Pitavastatin [Effect is not clinically significant – no dosage adjustment is necessary] | 1.24 (1.17, 1.31) | 0.977 (0.841, 1.14)
Rosiglitazone | 4 mg single oral dose | IVA 150 mg twice daily | ↔ Rosiglitazone | 0.975 (0.897, 1.06) | 0.928 (0.858, 1.00)
Desipramine | 50 mg single dose | IVA 150 mg twice daily | ↔ Desipramine | 1.04 (0.985, 1.10) | 1.00 (0.939, 1.07)
↑ = increase, ↓ = decrease, ↔ = no change. CI = Confidence interval; TEZ = tezacaftor; IVA = ivacaftor; PK = Pharmacokinetics

Table 10: Impact of Other Drugs on Tezacaftor/Ivacaftor or Ivacaftor
 | Dose and Schedule |  |  | Mean Ratio (90% CI) of Tezacaftor and Ivacaftor No Effect = 1.0
Drug | Dose | TEZ/IVA or IVA | Effect on TEZ/IVA PK | AUC | Cmax
Itraconazole | 200 mg twice a day on Day 1, followed by 200 mg once daily | TEZ 25 mg + IVA 50 mg once daily | ↑ Tezacaftor | 4.02 (3.71, 4.63) | 2.83 (2.62, 3.07)
Itraconazole | 200 mg twice a day on Day 1, followed by 200 mg once daily | TEZ 25 mg + IVA 50 mg once daily | ↑ Ivacaftor | 15.6 (13.4, 18.1) | 8.60 (7.41, 9.98)
Ciprofloxacin | 750 mg twice daily | TEZ 50 mg + IVA 150 mg twice daily | ↔ Tezacaftor | 1.08 (1.03, 1.13) | 1.05 (0.99, 1.11)
Ciprofloxacin | 750 mg twice daily | TEZ 50 mg + IVA 150 mg twice daily | ↑ Ivacaftor [Effect is not clinically significant – no dosage adjustment is necessary] | 1.17 (1.06, 1.30) | 1.18 (1.06, 1.31)
Oral Contraceptive | Norethindrone/ethinyl estradiol 1.0 mg/0.035 mg once daily | TEZ 100 mg/IVA 150 mg every morning + IVA 150 mg every evening | ↔ Tezacaftor | 1.01 (0.963, 1.05) | 1.01 (0.933, 1.09)
Oral Contraceptive | Norethindrone/ethinyl estradiol 1.0 mg/0.035 mg once daily | TEZ 100 mg/IVA 150 mg every morning + IVA 150 mg every evening | ↔ Ivacaftor | 1.03 (0.960, 1.11) | 1.03 (0.941, 1.14)
Rifampin | 600 mg once daily | IVA 150 mg single dose | ↓ Ivacaftor | 0.114 (0.097, 0.136) | 0.200 (0.168, 0.239)
Fluconazole | 400 mg single dose on Day 1, followed by 200 mg once daily | IVA 150 mg twice daily | ↑ Ivacaftor | 2.95 (2.27, 3.82) | 2.47 (1.93, 3.17)
↑ = increase, ↓ = decrease, ↔ = no change. CI = Confidence interval; TEZ = tezacaftor; IVA = ivacaftor; PK = Pharmacokinetics

13 NONCLINICAL TOXICOLOGY

13.1 Carcinogenesis, Mutagenesis, Impairment of Fertility

No studies of carcinogenicity, mutagenicity, or impairment of fertility were conducted with the combination of tezacaftor and ivacaftor, however, separate studies of tezacaftor and ivacaftor are described below.

Tezacaftor

A 2-year study in Sprague-Dawley rats and a 6-month study in Tg.rasH2 transgenic mice were conducted to assess the carcinogenic potential of tezacaftor. No evidence of tumorigenicity from tezacaftor was observed in male and female rats at oral doses up to 50 and 75 mg/kg/day (approximately 2 and 3 times the MRHD based on summed AUCs of tezacaftor and its metabolites in males and females, respectively). No evidence of tumorigenicity was observed in male and female Tg.rasH2 transgenic mice at tezacaftor doses up to 500 mg/kg/day.

Tezacaftor was negative for genotoxicity in the following assays: Ames test for bacterial gene mutation, in vitro chromosomal aberration assay in Chinese hamster ovary cells, and in vivo mouse micronucleus test.

There were no effects on male or female fertility and early embryonic development in rats at oral tezacaftor doses up to 100 mg/kg/day (approximately 3 times the MRHD based on summed AUC of tezacaftor and M1 metabolite).

Ivacaftor

Two-year studies were conducted in CD-1 mice and Sprague-Dawley rats to assess the carcinogenic potential of ivacaftor. No evidence of tumorigenicity from ivacaftor was observed in mice or rats at oral doses up to 200 mg/kg/day and 50 mg/kg/day, respectively (approximately equivalent to 2 and 9 times the MRHD, respectively, based on summed AUCs of ivacaftor and its metabolites).

Ivacaftor was negative for genotoxicity in the following assays: Ames test for bacterial gene mutation, in vitro chromosomal aberration assay in Chinese hamster ovary cells, and in vivo mouse micronucleus test.

Ivacaftor impaired fertility and reproductive performance indices in male and female rats at 200 mg/kg/day (approximately 9 and 6 times, respectively, the MRHD based on summed AUCs of ivacaftor and its metabolites). Increases in prolonged diestrus were observed in females at 200 mg/kg/day. Ivacaftor also increased the number of females with all nonviable embryos and decreased corpora lutea, implantations, and viable embryos in rats at 200 mg/kg/day (approximately 6 times the MRHD based on summed AUCs of ivacaftor and its metabolites) when dams were dosed prior to and during early pregnancy. These impairments of fertility and reproductive performance in male and female rats at 200 mg/kg/day were attributed to severe toxicity. No effects on male or female fertility and reproductive performance indices were observed at ≤100 mg/kg/day (approximately 6 and 4 times, respectively, the MRHD based on summed AUCs of ivacaftor and its metabolites).

14 CLINICAL STUDIES

Dose Ranging:

Dose selection for the clinical program primarily consisted of one double-blind, placebo-controlled, multiple-cohort trial which included 176 patients with CF (homozygous for the F508del mutation) 18 years of age and older with a screening ppFEV1≥40. In the study, 34 and 106 patients, respectively, received tezacaftor at once-daily doses of 10 mg, 30 mg, 100 mg, or 150 mg alone or in combination with ivacaftor 150 mg q12h, and 33 patients received placebo. During the 28-day treatment period, dose-dependent increases in mean ppFEV1 change from baseline were observed with tezacaftor in combination with ivacaftor. Tezacaftor/ivacaftor in general had a greater mean treatment effect than tezacaftor alone. No additional benefit was observed at tezacaftor doses greater than 100 mg daily.

Efficacy:

The efficacy of SYMDEKO in patients with CF aged 12 years and older was evaluated in three double-blind, placebo-controlled trials (Trials1, 2, and 3).

Trial 1 was a 24-week randomized, double-blind, placebo-controlled, two-arm study in patients with CF who were homozygous for the F508del mutation in the CFTR gene.

Trial 2 was a randomized, double-blind, placebo-controlled, 2-period, 3-treatment, 8-week crossover study in patients with CF who were heterozygous for the F508del mutation and a second mutation predicted to be responsive to tezacaftor/ivacaftor. Mutations predicted to be responsive were selected for the study based on the clinical phenotype (pancreatic sufficiency), biomarker data (sweat chloride), and in vitro responsiveness to tezacaftor/ivacaftor [see Clinical Studies (14.2)]. Patients were randomized to and received sequences of treatment that included SYMDEKO, ivacaftor, and placebo.

Trial 3 was a 12-week randomized, double-blind, placebo-controlled, two-arm study in patients with CF who were heterozygous for the F508del mutation and a second CFTR mutation predicted to be unresponsive to tezacaftor/ivacaftor. Mutations predicted to be non-responsive were selected for the study based on biologic plausibility (mutation class), clinical phenotype (pancreatic insufficiency), biomarker data (sweat chloride), and in vitro testing to tezacaftor and/or ivacaftor.

Patients in all trials continued on their standard-of-care CF therapies (e.g., bronchodilators, inhaled antibiotics, dornase alfa, and hypertonic saline) and were eligible to roll over into a 96-week open-label extension. Patients had a ppFEV1 at screening between 40-90%. Patients with a history of colonization with organisms associated with a more rapid decline in pulmonary status such as Burkholderia cenocepacia, Burkholderia dolosa, or Mycobacterium abscessus, or who had 2 or more abnormal liver function tests at screening (ALT, AST, AP, GGT ≥3 × ULN or total bilirubin ≥2 × ULN) or AST or ALT ≥5 × ULN, were excluded from the trials.

14.1 Trial in Patients with CF Who Were Homozygous for the F508del Mutation in the CFTR Gene (Trial 1)

Trial 1 evaluated 504 patients (248 SYMDEKO, 256 placebo) with CF aged 12 years and older (mean age 26.3 years). The mean ppFEV1 at baseline was 60.0% (range: 27.8% to 96.2%). The primary efficacy endpoint was change in lung function as determined by absolute change from baseline in ppFEV1 through Week 24. Treatment with SYMDEKO resulted in a statistically significant improvement in ppFEV1. The treatment difference between SYMDEKO and placebo for the mean absolute change in ppFEV1 from baseline through Week 24 was 4.0 percentage points (95% CI: 3.1, 4.8; P<0.0001). These changes persisted throughout the 24-week treatment period (Figure 1). Improvements in ppFEV1 were observed regardless of age, sex, baseline ppFEV1, colonization with Pseudomonas, concomitant use of standard-of-care medications for CF, and geographic region.

Key secondary efficacy variables included relative change from baseline in ppFEV1 through Week 24; number of pulmonary exacerbations from baseline through Week 24; absolute change in BMI from baseline at Week 24, and absolute change in CFQ-R Respiratory Domain Score (a measure of respiratory symptoms relevant to patients with CF, such as cough, sputum production, and difficulty breathing) from baseline through Week 24. For the purposes of this trial, a pulmonary exacerbation was defined as a change in antibiotic therapy (IV, inhaled, or oral) as a result of 4 or more of 12 pre-specified sino-pulmonary signs/symptoms. See Table 11 for a summary of key secondary outcomes in Trial 1.

Table 11: Key Secondary Efficacy Analyses, Full Analysis Set (Trial 1) [A hierarchical testing procedure was performed for primary and secondary endpoints vs placebo; at each step, P≤0.05 and all previous tests also meeting this level of significance were required for statistical significance.]
 |  | Placebo N=256 | SYMDEKO N=248
Relative change in ppFEV1 from baseline through Week 24 (%) | Treatment difference (95% CI) | - | 6.8 (5.3, 8.3)
Relative change in ppFEV1 from baseline through Week 24 (%) | P value | NA | P<0.0001 [Indicates statistical significance confirmed in the hierarchical testing procedure. Other efficacy measures considered not statistically significant.]
Number of pulmonary exacerbations from baseline through Week 24 | Number of events (event rate per year [Estimated event rate per year calculated using 48 weeks per year.]) Rate ratio (95% CI) | 122 (0.99) | 78 (0.64) 0.65 (0.48, 0.88)
Number of pulmonary exacerbations from baseline through Week 24 | P value | NA | P=0.0054
Absolute change in BMI from baseline at Week 24 (kg/m^2) | Treatment difference (95% CI) | - | 0.06 (-0.08, 0.19)
Absolute change in CFQ-R Respiratory Domain Score from baseline through Week 24 (points) | Treatment difference (95% CI) | - | 5.1 (3.2, 7.0)
BMI: body mass index; CI: confidence interval; CFQ-R: Cystic Fibrosis Questionnaire-Revised; IVA: ivacaftor; NA: not applicable; ppFEV1: percent predicted forced expiratory volume in 1 second;

Figure 1: Absolute Change From Baseline in Percent Predicted FEV1 at Each Visit in Trial 1

14.2 Trial in Patients with CF Who Were Heterozygous for the F508del Mutation and a Second Mutation Predicted to be Responsive to Tezacaftor/Ivacaftor (Trial 2)

Trial 2 evaluated 244 patients with CF aged 12 years and older (mean age 34.8 years). The mean ppFEV1 at baseline was 62.3% (range: 34.6 to 93.5). Of the 244 patients included in the efficacy analysis, 146 patients had a splice mutation and 98 patients had a missense mutation as the second allele. 161 patients received SYMDEKO, 156 patients received ivacaftor, and 161 patients received placebo. The primary efficacy endpoint was the mean absolute change from study baseline in percent predicted FEV1 averaged at Weeks 4 and 8 of treatment. The key secondary efficacy endpoint was absolute change in CFQ-R Respiratory Domain Score from study baseline averaged at Weeks 4 and 8 of treatment. For the overall population, treatment with SYMDEKO compared to placebo resulted in significant improvement in ppFEV1 (6.8 percentage points [95% CI: 5.7, 7.8]; P<0.0001) and CFQ-R Respiratory Domain Score (11.1 points (95% CI: 8.7, 13.6); P<0.0001). Treatment difference for ppFEV1 between ivacaftor- and placebo-treated patients was 4.7 percentage points (95% CI: 3.7, 5.8; P<0.0001) and 2.1 percentage points (95% CI: 1.2, 2.9; P<0.0001) between SYMDEKO- and ivacaftor-treated patients, which were statistically significant. Improvements in ppFEV1 were observed regardless of age, baseline ppFEV1, sex, mutation class, colonization with Pseudomonas, concomitant use of standard-of-care medications for CF, and geographic region. Statistically significant improvements compared to placebo were also observed in the subgroup of patients with splice mutations and missense mutations (Table 12).

Table 12: Effect of SYMDEKO for Efficacy Variables in Splice and Missense CFTR Mutation Subgroups
Mutation (n) | Absolute Change in percent predicted FEV1 [Average of Week 4 and 8 values.] [Absolute change in ppFEV1 by individual mutations is an ad hoc analysis.] | Absolute Change in CFQ-R Respiratory Domain Score (Points) [Absolute change in CFQ-R Respiratory Domain Score and absolute change in sweat chloride by mutation subgroups and by individual mutations are ad hoc analyses.] | Absolute Change in Sweat Chloride (mmol/L)
Splice mutations (n= 93 for TEZ/IVA, n=97 for PBO)
Results shown as difference in mean (95% CI) change from study baseline for SYMDEKO vs. placebo-treated patients:
 | 7.4 (6.0, 8.7) | 9.5 (6.3, 12.7) | -5.4 (-8.0, -2.7)
By individual splice mutation (n). Results shown as mean (minimum, maximum) for change from study baseline for SYMDEKO-treated patients
2789+5G→A (25) | 8.6 (-1.5, 23.4) | 12.0 (-8.3, 38.9) | -3.2 (-16.5, 9.0)
3272-26A→G (23) | 5.7 (-2.1, 25.9) | 5.7 (-22.2, 44.4) | -3.8 (-22.3, 16.5)
3849+10kbC→T (43) | 5.8 (-7.2, 22.3) | 8.2 (-25.0, 47.2) | -5.6 (-27.0, 8.5)
711+3A→G (2) | 4.3 (2.0, 6.7) | -4.2 (-5.6, -2.8) | -15.4 (-21.0, -9.8)
E831X [Patients enrolled did not receive tezacaftor/ivacaftor treatment.] (0) | NA | NA | NA
Missense mutations (n=66 for TEZ/IVA, n=63 for PBO)
Results shown as difference in mean (95% CI) change from study baseline for SYMDEKO vs. placebo-treated patients:
 | 5.9 (4.2, 7.5) | 13.4 (9.6, 17.3) | -16.3 (-19.7, -12.9)
By individual missense mutation (n). Results shown as mean (minimum, maximum) for change from study baseline for SYMDEKO-treated patients
D579G (2) | 8.1 (-0.2, 16.4) | 11.1 (5.6, 16.7) | -23.1 (-24.8, -21.5)
D110H (1) | -1.0 (-1.0, -1.0) | -11.1 (-11.1, -11.1) | -22.5 (-22.5, -22.5)
D1152H (21) | 3.8 (-2.5, 12.5) | 15.2 (-8.3, 55.6) | -4.1 (-15.0, 11.5)
A455E (11) | 8.5 (2.6, 16.1) | 11.6 (-11.1, 44.4) | -0.3 (-8.8, 14.0)
L206W (4) | 3.0 (-4.5, 10.2) | 12.5 (-2.8, 38.9) | -36.1 (-44.5, -27.5)
P67L (11) | 9.4 (0.0, 31.9) | 11.7 (-12.5, 72.2) | -29.3 (-50.0, 0.8)
R1070W (2) | 6.1 (2.0, 10.1) | 29.2 (16.7, 41.7) | -13.8 (-26.8, -0.8)
R117C (1) | 2.9 (2.9, 2.9) | 16.7 (16.7, 16.7) | -38.8 (-38.8, -38.8)
R347H (2) | -0.5 (-2.8, 1.7) | 5.6 (-5.6, 16.7) | -13.8 (-19.0, -8.5)
R352Q (2) | 4.9 (2.6, 7.1) | 8.3 (8.3, 8.3) | -43.3 (-49.8, -36.8)
S945L (7) | 9.6 (0.7, 19.5) | 11.3 (-4.2, 25.0) | -29.0 (-42.5, -8.0)
S977F (2) | 10.1 (5.5, 14.7) | -1.4 (-8.3, 5.6) | -13.9 (-22.3, -5.5)
(n=) patient numbers analysed.

In an analysis of BMI at Week 8, an exploratory endpoint, patients treated with SYMDEKO had a mean improvement of 0.2 kg/m^2 (95% CI [0.0, 0.3]), 0.1 kg/m^2 (95% CI [-0.1, 0.3]), and 0.3 kg/m^2 (95% CI [0.1, 0.5]) versus placebo for the overall, splice, and missense mutation populations of patients, respectively.

14.3 Trial in Patients with CF Who Were Heterozygous for the F508del Mutation and a Second Mutation Not Predicted to be Responsive to Tezacaftor/Ivacaftor (Trial 3)

Trial 3 evaluated 168 patients with CF (83 SYMDEKO and 85 placebo) aged 12 years and older (mean age 26.1 years) who were heterozygous for the F508del mutation and had a second CFTR mutation predicted to be unresponsive to tezacaftor/ivacaftor. CF patients with the F508del mutation and one of the following mutations in the CFTR gene were enrolled in the study (listed in decreasing frequency): W1282X, G542X, N1303K, 621+1G>T, 1717-1G>A, 1898+1G>A, CFTRdele2,3, 2183delAA>G, 2184insA, R1162X, R553X, 3659delC, 3905insT, G970R, I507del, R1066C, R347P, 1154insTC, 1811+1.6kbA>G, 2184delA, 405+1G>A, E60X, G85E, L1077P, Q39X, S466X, Y1092X, 1078delT, 1248+1G>A, 1677delTA, 1812-1G>A, 2869INSG, 3120+1G>A, 394delTT, 457TAT>G, 711+1G>T, 711+5G>A, 712-1G>T, G673x, L1065P, Q220X, Q493X, R709X, V520F. The mean ppFEV1 at baseline was 57.5% [range: 31.0 to 96.7]. The primary efficacy endpoint was changed from baseline in absolute ppFEV1 through Week 12. The overall treatment difference between SYMDEKO and placebo for the mean absolute change in ppFEV1 from baseline through Week 12 was 1.2 percentage points (95% CI: -0.3, 2.6). This study was terminated following the planned interim analysis because the pre-specified futility criteria were met.

16 HOW SUPPLIED/STORAGE AND HANDLING

SYMDEKO (tezacaftor 50 mg/ivacaftor 75 mg fixed-dose combination tablets co-packaged with ivacaftor 75 mg tablet):

- Tezacaftor 50 mg/ivacaftor 75 mg fixed-dose combination tablets are supplied as white, oblong-shaped tablets containing 50 mg of tezacaftor and 75 mg of ivacaftor. Each tablet is debossed with "V50" on one side and plain on the other.
- Ivacaftor 75 mg tablets are supplied as light blue, film-coated, oblong-shaped tablets containing 75 mg of ivacaftor. Each tablet is printed with the characters "V 75" on one side and plain on the other.
- 56-count tablet carton containing a 4-week supply (4 weekly wallets, each with 14 tablets) NDC 51167-113-01

SYMDEKO (tezacaftor 100 mg/ivacaftor 150 mg fixed-dose combination tablets co-packaged with ivacaftor 150 mg tablet):

- Tezacaftor 100 mg/ivacaftor 150 mg fixed-dose combination tablets are supplied as yellow, oblong-shaped tablets containing 100 mg of tezacaftor and 150 mg of ivacaftor. Each tablet is debossed with "V100" on one side and plain on the other.
- Ivacaftor 150 mg tablets are supplied as light blue, film-coated, oblong-shaped tablets containing 150 mg of ivacaftor. Each tablet is printed with the characters "V 150" on one side and plain on the other.
- 56-count tablet carton containing a 4-week supply (4 weekly wallets, each with 14 tablets) NDC 51167-661-01

STORAGE AND HANDLING

Store at 68°F to 77°F (20°C to 25°C); excursions permitted to 59°F to 86°F (15°C to 30°C) [see USP Controlled Room Temperature].

17 PATIENT COUNSELING INFORMATION

Advise the patient to read the FDA-approved patient labeling (Patient Information).

Transaminase (ALT or AST) Elevations and Monitoring

Inform patients that elevation in liver tests has occurred in patients treated with SYMDEKO or with ivacaftor alone. Transaminases (ALT and AST) should be assessed prior to initiating SYMDEKO, every 3 months during the first year of treatment, and annually thereafter. More frequent monitoring should be considered in patients with a history of transaminase elevations [see Warnings and Precautions (5.1)].

Hypersensitivity Reactions, Including Anaphylaxis

Hypersensitivity reactions including anaphylaxis are possible with use of SYMDEKO. Inform patients of the early signs of hypersensitivity reactions including rash, hives, itching, facial swelling, tightness of the chest and wheezing. Advise patients to discontinue use of SYMDEKO immediately and contact their physician or go to the emergency department if these symptoms occur.

Intracranial Hypertension

Inform patients that intracranial hypertension has occurred in patients who received drugs containing the same or similar active ingredients as SYMDEKO. Instruct patients to notify their healthcare provider right away if they experience signs and symptoms of intracranial hypertension, including headache, blurred vision, diplopia, and vision loss [see Warnings and Precautions (5.3)].

Drug Interactions with CYP3A Inducers and Inhibitors

Ask patients to tell you all the medications they are taking including any herbal supplements or vitamins. Co-administration of SYMDEKO with strong CYP3A inducers (e.g., rifampin, St. John's wort) is not recommended, as they may reduce the therapeutic effectiveness of SYMDEKO. Adjustment of the dosage to one tablet of tezacaftor/ivacaftor twice a week, taken approximately 3 to 4 days apart is recommended when co-administered with strong CYP3A inhibitors, such as ketoconazole. Advise the patient not to take the evening dose of ivacaftor. Dosage reduction to one tablet of tezacaftor/ivacaftor or ivacaftor, taken on alternate days in the morning is recommended when co-administered with moderate CYP3A inhibitors, such as fluconazole. Advise the patient not to take the evening dose of ivacaftor. Food or drink containing grapefruit should be avoided [see Warnings and Precautions (5.4), Drug Interactions (7), and Clinical Pharmacology (12.3)].

Cataracts

Inform patients that abnormality of the eye lens (cataract) has been noted in some children and adolescents receiving SYMDEKO or with ivacaftor alone. Baseline and follow-up ophthalmological examinations should be performed in pediatric patients initiating treatment with SYMDEKO [see Warnings and Precautions (5.5)].

Use in Patients with Hepatic Impairment

Inquire and/or assess whether patients have liver impairment. Adjust the dosage in patients with moderately impaired hepatic function (Child-Pugh Class B, score 7-9) to one tablet of tezacaftor/ivacaftor once daily in the morning and advise the patient not to take the evening dose of ivacaftor. SYMDEKO has not been studied in patients with severe hepatic impairment (Child-Pugh Class C, score 10-15); however, exposure is expected to be substantially higher than that observed in patients with moderate hepatic impairment. When benefits are expected to outweigh the risks, SYMDEKO should be used with caution in patients with severe hepatic impairment at a dosage of one tablet of tezacaftor/ivacaftor once daily in the morning or less frequently. Advise the patient not to take the evening dose of ivacaftor. No dosage adjustment is recommended for patients with mild hepatic impairment (Child-Pugh Class A, score 5-6) [see Dosage and Administration (2.3), Use in Specific Populations (8.6), and Clinical Pharmacology (12.3)].

Driving and Operating Machinery

Dizziness has been reported in patients receiving SYMDEKO, which could influence the ability to drive or operate machines [see Adverse Reactions (6.1)]. Advise patients not to drive or operate machines if they experience dizziness until symptoms abate.

Administration

Inform patients that SYMDEKO is best absorbed by the body when taken with food that contains fat. A typical CF diet will satisfy this requirement. Examples include eggs, butter, peanut butter, cheese pizza, whole-milk dairy products (such as whole milk, cheese, and yogurt), etc. [see Dosage and Administration (2.1) and Clinical Pharmacology (12.3)].

Patients should be informed about what to do in the event they miss a dose of SYMDEKO or ivacaftor:

- If 6 hours or less have passed since the time SYMDEKO is usually taken, patients should be instructed to take the prescribed dose of SYMDEKO with fat-containing food as soon as possible.
- If more than 6 hours have passed since the time SYMDEKO is usually taken, the missed dose should NOT be taken, and the patient should resume the recommended dosing schedule.
- Patients should be advised to contact their health care provider if they have questions.

Manufactured for
Vertex Pharmaceuticals Incorporated
50 Northern Avenue
Boston, MA 02210

SYMDEKO, VERTEX, and the VERTEX triangle logo are registered trademarks of Vertex Pharmaceuticals Incorporated.
All other trademarks referenced herein are the property of their respective owners.
©2025 Vertex Pharmaceuticals Incorporated
ALL RIGHTS RESERVED

PATIENT INFORMATION
SYMDEKO (SIM-deh-koh)
(tezacaftor/ivacaftor tablets; ivacaftor tablets)
for oral use

What is SYMDEKO?

- SYMDEKO is a prescription medicine used for the treatment of cystic fibrosis (CF) in patients aged 6 years and older who have two copies of the F508del mutation, or who have at least one mutation in the CF gene that is responsive to treatment with SYMDEKO.
- Talk to your doctor to learn if you have an indicated CF gene mutation.

It is not known if SYMDEKO is safe and effective in children under 6 years of age.

Before taking SYMDEKO, tell your doctor about all of your medical conditions, including if you:

- have or have had liver problems.
- are allergic to SYMDEKO or any ingredients in SYMDEKO. See the end of this patient information leaflet for a complete list of ingredients in SYMDEKO.
- have kidney problems.
- are pregnant or plan to become pregnant. It is not known if SYMDEKO will harm your unborn baby. You and your doctor should decide if you will take SYMDEKO while you are pregnant.
- are breastfeeding or planning to breastfeed. It is not known if SYMDEKO passes into your breast milk. You and your doctor should decide if you will take SYMDEKO while you are breastfeeding.

Tell your doctor about all the medicines you take, including prescription and over-the-counter medicines, vitamins, and herbal supplements,
SYMDEKO may affect the way other medicines work and other medicines may affect how SYMDEKO works. The dosage of SYMDEKO may need to be adjusted when taken with certain medicines. Ask your doctor or pharmacist for a list of these medicines if you are not sure.
Especially tell your doctor if you take:

- antibiotics such as rifampin (RIFAMATE®, RIFATER®) or rifabutin (MYCOBUTIN®)
- seizure medicines such as phenobarbital, carbamazepine (TEGRETOL®, CARBATROL®, EQUETRO®), or phenytoin (DILANTIN®, PHENYTEK®)
- St. John's wort
- antifungal medicines such as ketoconazole, itraconazole (such as SPORANOX®), posaconazole (such as NOXAFIL®), voriconazole (such as VFEND®), or fluconazole (such as DIFLUCAN®)
- antibiotics such as telithromycin, clarithromycin (e.g., BIAXIN®), or erythromycin (such as ERY-TAB®)

Know the medicines you take. Keep a list of them to show your doctor and pharmacist when you get a new medicine.

How should I take SYMDEKO?

- Take SYMDEKO exactly as your doctor tells you to take it.
- Take SYMDEKO by mouth only.
- Always take SYMDEKO with food that contains fat. Examples of fat-containing foods include eggs, butter, peanut butter, cheese pizza, and whole-milk dairy products such as whole milk, cheese, and yogurt.
- SYMDEKO consists of 2 different tablets.
- SYMDEKO Tablets (age 6 to less than 12 years weighing less than 30 kg):
  - The white tablet is marked with 'V50' and contains the medicines tezacaftor and ivacaftor. Take 1 white tablet in the morning.
  - The light blue tablet is marked with 'V 75' and contains the medicine ivacaftor. Take 1 light blue tablet in the evening.
- SYMDEKO Tablets (age 6 to less than 12 years weighing 30 kg or more and age 12 years and older):
  - The yellow tablet is marked with 'V100' and contains the medicines tezacaftor and ivacaftor. Take 1 yellow tablet in the morning.
  - The light blue tablet is marked with 'V 150' and contains the medicine ivacaftor. Take 1 light blue tablet in the evening.
- Take the morning and the evening tablet about 12 hours apart.
- If you miss a dose of SYMDEKO and:
  - it is 6 hours or less from the time you usually take the yellow tablet in the morning or the light blue tablet in the evening, take the missed dose with food that contains fat as soon as you can. Then take your next dose at your usual time.
  - it is more than 6 hours from the time you usually take the yellow tablet in the morning or the light blue tablet in the evening, do not take the missed dose. Take your next dose at the usual time with food that contains fat.
- Do not take more than your recommended dose of SYMDEKO to make up for a missed dose.

What should I avoid while taking SYMDEKO?

- SYMDEKO can cause dizziness in some people who take it. If you experience dizziness, do not drive or operate machines until symptoms improve.
- Avoid food or drink that contains grapefruit while you are taking SYMDEKO.

What are the possible side effects of SYMDEKO?
SYMDEKO can cause serious side effects, including:

- High liver enzymes in the blood have been reported in people treated with SYMDEKO or treated with ivacaftor alone. Your doctor will do blood tests to check your liver:
  - before you start SYMDEKO
  - every 3 months during your first year of taking SYMDEKO
  - every year while you are taking SYMDEKO

Your doctor may do blood tests to check the liver more often if you have had high liver enzymes in your blood in the past.
Call your doctor right away if you have any of the following symptoms of liver problems:

- pain or discomfort in the upper right stomach (abdominal) area
- yellowing of your skin or the white part of your eyes
- loss of appetite

- nausea or vomiting
- dark, amber-colored urine

- Serious Allergic Reactions can happen to people who are treated with SYMDEKO. Call your doctor or go to the emergency room right away if you have any symptoms of an allergic reaction. Symptoms of an allergic reaction may include:

- rash or hives
- tightness of the chest or throat or difficulty breathing

- light-headedness or dizziness

- Increased pressure around the brain (intracranial hypertension) has happened in people treated with medicines containing the same or similar ingredients as SYMDEKO. If you experience an unusual headache, blurred vision, double vision, or vision loss, call your doctor right away.
- Abnormality of the eye lens (cataract) in some children and adolescents treated with SYMDEKO or treated with ivacaftor alone. If you are a child or adolescent, your doctor should perform eye examinations before and during treatment with SYMDEKO to look for cataracts.

The most common side effects of SYMDEKO include:

- headache
- nausea

- sinus congestion
- dizziness

Tell your doctor if you have any side effect that bothers you or that does not go away.
These are not all the possible side effects of SYMDEKO. For more information, ask your doctor or pharmacist.
Call your doctor for medical advice about side effects. You may report side effects to FDA at 1-800-FDA-1088.

How should I store SYMDEKO?

- Store SYMDEKO at room temperature between 68°F to 77°F (20°C to 25°C).

Keep SYMDEKO and all medicines out of the reach of children.

General information about the safe and effective use of SYMDEKO.
Medicines are sometimes prescribed for purposes other than those listed in a Patient Information leaflet. Do not use SYMDEKO for a condition for which it was not prescribed. Do not give SYMDEKO to other people, even if they have the same symptoms you have. It may harm them.
You can ask your pharmacist or doctor for information about SYMDEKO that is written for health professionals.

What are the ingredients in SYMDEKO?
Tezacaftor/ivacaftor tablets:
Active ingredients: tezacaftor and ivacaftor
Inactive ingredients: hypromellose acetate succinate, sodium lauryl sulfate, hypromellose, microcrystalline cellulose, croscarmellose sodium, magnesium stearate, HPMC/hypromellose 2910, hydroxypropyl cellulose, titanium dioxide, talc, and iron oxide yellow (in tezacaftor 100 mg/ivacaftor 150 mg tablets only).
Ivacaftor tablets:
Active ingredient: ivacaftor
Inactive ingredients: colloidal silicon dioxide, croscarmellose sodium, hypromellose acetate succinate, lactose monohydrate, magnesium stearate, microcrystalline cellulose, sodium lauryl sulfate, carnauba wax, FD&C Blue #2, PEG 3350, polyvinyl alcohol, talc, titanium dioxide, ammonium hydroxide, iron oxide black, propylene glycol, and shellac.

Manufactured for: Vertex Pharmaceuticals Incorporated; 50 Northern Avenue, Boston, MA 02210
SYMDEKO, VERTEX and the VERTEX triangle logo are registered trademarks of Vertex Pharmaceuticals Incorporated.
All other trademarks referenced herein are the property of their respective owners.
©2025 Vertex Pharmaceuticals Incorporated
For more information, go to www.symdeko.com or call 1-877-752-5933.

This Patient Information has been approved by the U.S. Food and Drug Administration.

Revised: 09/2025

PRINCIPAL DISPLAY PANEL - Kit Carton

Rx Only
NDC 51167-661-01

symdeko®
(tezacaftor/ivacaftor) 100 mg/150 mg
and (ivacaftor) 150 mg tablets

56 tablets
Contains 4-week supply of SYMDEKO
4 weekly blister cards, each with 14 tablets:
(7 tezacaftor/ivacaftor and 7 ivacaftor tablets)

LIFT HERE TO OPEN ▶

PRINCIPAL DISPLAY PANEL - Kit Carton - 113

Rx Only
NDC 51167-113-01

symdeko®

(tezacaftor/ivacaftor) 50 mg/75 mg
and (ivacaftor) 75 mg tablets

56 tablets

Contains 4-week supply of SYMDEKO
4 weekly blister cards, each with 14 tablets:
(7 tezacaftor/ivacaftor and 7 ivacaftor tablets)

LIFT HERE TO OPEN ▶